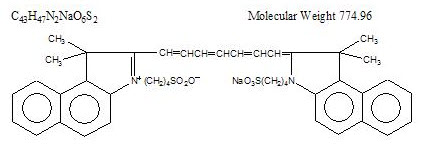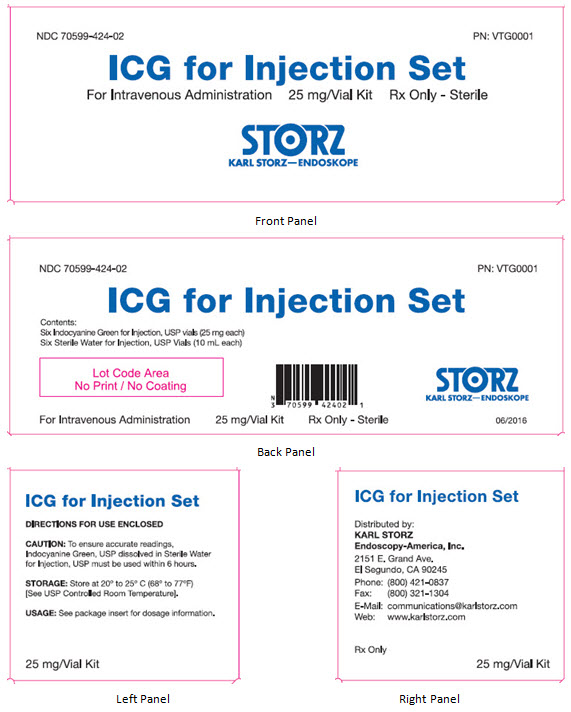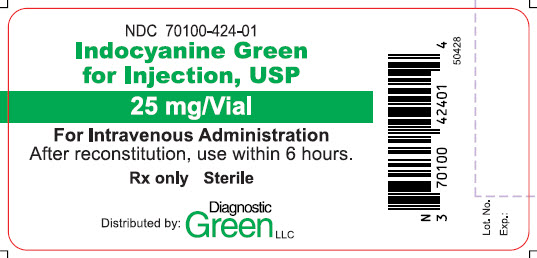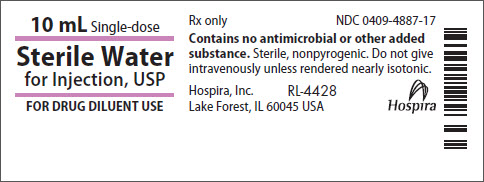 DRUG LABEL: ICG
NDC: 70599-424 | Form: KIT | Route: INTRAVENOUS
Manufacturer: KARL STORZ Endoscopy-America, Inc.
Category: prescription | Type: HUMAN PRESCRIPTION DRUG LABEL
Date: 20201113

ACTIVE INGREDIENTS: INDOCYANINE GREEN 25 mg/1 1; WATER 1 mL/1 mL
INACTIVE INGREDIENTS: SODIUM IODIDE

HIGHLIGHTS OF PRESCRIBING INFORMATION

These highlights do not include all the information needed to use ICG for Injection Set safely and effectively. See full prescribing information for Indocyanine Green for Injection, USP.
Initial U.S. Approval: 1959

1 INDICATIONS AND USAGE

ICG for Injection Set, a tricarbocyanine dye, is indicated for use with the KARL STORZ ICG Imaging System to provide real-time endoscopic visible and near-infrared fluorescence imaging. ICG for Injection Set used in conjunction with the KARL STORZ ICG Imaging System enables surgeons to perform minimally invasive surgery using standard endoscopic visible light as well as:

- Visual assessment of vessels, blood flow and related tissue perfusion. (1.1)
- Visual assessment of at least one of the major extra-hepatic bile ducts (cystic duct, common bile duct and common hepatic duct), using near-infrared imaging. Fluorescence imaging of biliary ducts with the KARL STORZ ICG Imaging System is intended for use with standard of care white light and, when indicated, intraoperative cholangiography. The device is not intended for standalone use for biliary duct visualization. (1.2)

2 DOSAGE AND ADMINISTRATION

Perfusion Assessment (2.1)

Under sterile conditions, reconstitute one (1) 25 mg vial of Indocyanine Green for Injection, USP using one (1) 10 mL Sterile Water for Injection, USP vial located in the ICG for Injection Set. Shake the ICG vial gently to dissolve. After reconstitution, a 25 mg vial of ICG contains 2.5 mg of dye per mL of solution, so a 1.0 mL injection contains a 2.5 mg dose of ICG. ICG must be used within 6 hours after reconstitution.

A 3 mL (7.5 mg) dose, followed by a 10 mL bolus of saline, is recommended. Multiple doses can be administered as required.

Extra-Hepatic Biliary Anatomy (2.2)

Under sterile conditions, reconstitute one (1) 25 mg vial of Indocyanine Green for Injection, USP using one (1) 10 mL Sterile Water for Injection, USP vial located in the ICG for Injection Set. Shake the ICG vial gently to dissolve. After reconstitution, a 25 mg vial of ICG contains 2.5 mg of dye per mL of solution, so a 1.0 mL injection contains a 2.5 mg dose of ICG. ICG must be used within 6 hours after reconstitution.

A 0.02 mL/kg dose that is scaled to the patient’s weight, followed by a 10 mL bolus of saline, is recommended. This provides 0.05 mg/kg of ICG.

3 DOSAGE FORMS AND STRENGTHS

Indocyanine Green for Injection, USP is a sterile, lyophilized green powder containing 25 mg of indocyanine green with no more than 5% sodium iodide. (3)

4 CONTRAINDICATIONS

Indocyanine Green for Injection, USP contains sodium iodide and should be used with caution in patients who have a history of allergy to iodides because of the risk of anaphylaxis. (4)

5 WARNINGS AND PRECAUTIONS

- Deaths due to anaphylaxis have been reported following Indocyanine Green for Injection, USP administration during cardiac catheterization. (5.1)
- Indocyanine Green for Injection, USP is unstable in aqueous solution and must be used within 6 hours. (5.2)
- Radioactive iodine uptake studies should not be performed for at least a week following the use of Indocyanine Green for Injection, USP. (5.3)

6 ADVERSE REACTIONS

Most common adverse reactions are anaphylactic or urticarial reactions. These have been reported in patients with and without a history of allergy to iodides. (6)

To report SUSPECTED ADVERSE REACTIONS, contact Diagnostic Green LLC at 1-844-424-3784 (1-844-ICG-DRUG) or e-mail: drugsafety@diagnosticgreen.com; or FDA at 1-800-FDA-1088 or www.fda.gov/medwatch.

7 DRUG INTERACTIONS

Products containing sodium bisulfite reduce the absorption peak of Indocyanine Green for Injection, USP in blood. (7)

FULL PRESCRIBING INFORMATION

1 INDICATIONS AND USAGE

ICG for Injection Set, a tricarbocyanine dye, is indicated for use with the KARL STORZ ICG Imaging System to provide real-time endoscopic visible and near-infrared fluorescence imaging. Indocyanine Green for Injection, USP used in conjunction with the KARL STORZ ICG Imaging System enables surgeons to perform minimally invasive surgery using standard endoscopic visible light as well as:

1.2 Visual assessment of at least one of the major extra-hepatic bile ducts (cystic duct, common bile duct and common hepatic duct), using near-infrared imaging.

Visual assessment of at least one of the major extra-hepatic bile ducts (cystic duct, common bile duct and common hepatic duct), using near-infrared imaging. Fluorescence imaging of biliary ducts with the KARL STORZ ICG Imaging System is intended for use with standard of care white light and, when indicated, intraoperative cholangiography. The device is not intended for standalone use for biliary duct visualization.

2 DOSAGE AND ADMINISTRATION

2.1 Perfusion Assessment

Preparation of ICG for Administration

Under sterile conditions, reconstitute one (1) 25 mg vial of Indocyanine Green for Injection, USP using one (1) 10 mL Sterile Water for Injection, USP vial located in the ICG for Injection Set. Shake the ICG vial gently to dissolve. After reconstitution, a 25 mg vial of ICG contains 2.5 mg of dye per mL of solution, so a 1.0 mL injection contains a 2.5 mg dose of ICG.

Indocyanine Green for Injection, USP must be used within 6 hours after reconstitution. If a precipitate is present, discard the solution.

Dosage

A 3 mL (7.5 mg) dose followed by a 10 mL bolus of saline is recommended. Multiple doses can be administered as required, up to the maximum recommended dose.

Maximum recommended dose

The total dose of dye injected should be kept below 2 mg/kg.

Timing of ICG Administration

ICG fluorescence is quickly visible within blood vessels, tissue and organs, and it does not last very long (refer to Table 1 below).

Table 1: ICG fluorescence visibility after intravenous injection
 | Blood Vessels | Organs (Kidney, Liver, Adrenal Gland, Small Bowel)
See within: | 5-30 seconds | 1-2 minutes
Visibility lasts: | 20-30 seconds | 20-120 minutes

For fluorescence imaging of PERFUSION in blood vessels, administration of the ICG should be performed at the time fluorescence imaging is requested by the physician. Multiple imaging sequences may be performed as necessary [up to the maximum dose (2 mg/kg of patient body weight)], so it is recommended to withdraw the desired dosage of ICG solution for each planned imaging sequence into separate syringes ahead of time.

Method of Administration

ICG administration is to be performed via a central or peripheral venous line. Inject the prepared dose of ICG solution into the central or peripheral line as a tight bolus and immediately followed by a bolus of 10-12 mL of normal saline for injection.

2.2 Extra-Hepatic Biliary Anatomy

Preparation of ICG for Administration

Under sterile conditions, reconstitute one (1) 25 mg vial of Indocyanine Green for Injection, USP using one (1) 10 mL Sterile Water for Injection, USP vial located in the ICG for Injection Set. Shake the ICG vial gently to dissolve. After reconstitution, a 25 mg vial of ICG contains 2.5 mg of dye per mL of solution, so a 1.0 mL injection contains a 2.5 mg dose of ICG.

Indocyanine Green for Injection, USP must be used within 6 hours after reconstitution. If a precipitate is present, discard the solution.

Dosage

A 0.02 mL/kg dose that is scaled to the patient’s weight is recommended. This provides 0.05 mg/kg of ICG.

Maximum recommended dose

The total dose of dye injected should be kept below 2 mg/kg.

Timing of ICG Administration

Following intravenous injection, ICG is rapidly bound to plasma protein, of which albumin is the principle carrier (95%). ICG is taken up from the plasma almost exclusively by the hepatic parenchymal cells and is secreted entirely into the bile. For optimal fluorescence imaging of Extra-Hepatic Biliary Anatomy, ICG should be administered at least 45 minutes prior to the time fluorescence imaging is desired by the physician. If this preoperative administration is not performed, however, ICG can be administered once the patient is in the OR, as adequate fluorescence imaging is possible in as little as 15 minutes after IV injection.

Method of Administration

ICG administration is to be performed via a central or peripheral venous line. Inject the prepared weight-scaled dose of ICG solution into the central or peripheral line as a tight bolus and immediately followed by a bolus of 10-12 mL of normal saline for injection.

3 DOSAGE FORMS AND STRENGTHS

Indocyanine Green for Injection, USP is a sterile, lyophilized green powder containing 25 mg of indocyanine green with no more than 5% sodium iodide.

4 CONTRAINDICATIONS

Indocyanine Green for Injection, USP contains sodium iodide and should be used with caution in patients who have a history of allergy to iodides because of the risk of anaphylaxis.

5 WARNINGS AND PRECAUTIONS

5.1 Anaphylaxis

Deaths from anaphylaxis have been reported following Indocyanine Green for Injection, USP administration during cardiac catheterization.

5.2 Drug Instability

Indocyanine Green for Injection, USP is unstable in aqueous solution and must be used within 6 hours. However, the dye is stable in plasma and whole blood so that samples obtained in discontinuous sampling techniques may be read hours later. Sterile techniques should be used in handling the dye solution as well as in the performance of the procedures. If a precipitate is present, discard the solution.

5.3 Drug/Laboratory Test Interactions

Radioactive iodine uptake studies should not be performed for at least a week following the use of Indocyanine Green for Injection, USP.

6 ADVERSE REACTIONS

Anaphylactic or urticarial reactions have been reported in patients with or without history of allergy to iodides. If such reactions occur, treat with the appropriate agents, e.g., epinephrine, antihistamines, and corticosteroids.

7 DRUG INTERACTIONS

Preparations containing sodium bisulfite, including some heparin products reduce the absorption peak of Indocyanine Green for Injection, USP in blood and, therefore, should not be used as an anticoagulant for the collection of samples for analysis.

8 USE IN SPECIFIC POPULATIONS

8.1 Pregnancy

Animal reproduction studies have not been conducted with Indocyanine Green for Injection, USP. It is also not known whether Indocyanine Green for Injection, USP can cause fetal harm when administered to a pregnant woman or can affect reproduction capacity. Indocyanine Green for Injection, USP should be given to a pregnant woman only if clearly indicated.

8.3 Nursing Mothers

It is not known whether this drug is excreted in human milk. Because many drugs are excreted in human milk, caution should be exercised when Indocyanine Green for Injection, USP is administered to a nursing woman.

8.4 Pediatric Use

Safety and effectiveness in pediatric patients have been established.

8.5 Geriatric Use

No overall differences in safety or effectiveness have been observed between elderly and younger patients.

10 OVERDOSAGE

There are no data available describing the signs, symptoms, or laboratory findings accompanying overdosage. The LD50 after intravenous administration ranges between 60 and 80 mg/kg in mice, 50 and 70 mg/kg in rats and 50 and 80 mg/kg in rabbits.

11 DESCRIPTION

Indocyanine Green for Injection, USP is a sterile, lyophilized green powder containing 25 mg of indocyanine green with no more than 5% sodium iodide. It is packaged with Sterile Water for Injection, USP used to dissolve the indocyanine green. Indocyanine Green for Injection, USP is to be administered intravenously.

Indocyanine green is a water soluble, tricarbocyanine dye with a peak spectral absorption at 800 nm. The chemical name for Indocyanine Green is 1 H-Benz[e]indolium, 2-[7-[1,3-dihydro-1,1-dimethyl-3-(4-sulfobutyl)-2H-benz[e] indol-2-ylidene]-1,3,5-heptatrienyl]-1,1-dimethyl-3-(4-sulfobutyl)-,hydroxide, inner salt, sodium salt. Indocyanine Green for Injection, USP has a pH of approximately 6.5 when reconstituted. Each vial of Indocyanine Green for Injection, USP contains 25 mg of indocyanine green as a sterile lyophilized powder.

12 CLINICAL PHARMACOLOGY

Following intravenous injection, Indocyanine Green for Injection, USP is rapidly bound to plasma protein, of which albumin is the principle carrier (95%). Indocyanine Green for Injection, USP undergoes no significant extrahepatic or enterohepatic circulation; simultaneous arterial and venous blood estimations have shown negligible renal, peripheral, lung or cerebro-spinal uptake of the dye. Indocyanine Green for Injection, USP is taken up from the plasma almost exclusively by the hepatic parenchymal cells and is secreted entirely into the bile.

The peak absorption and emission of Indocyanine Green for Injection, USP lie in a region (800 to 850 nm) where transmission of energy by the pigment epithelium is more efficient than in the region of visible light energy. Indocyanine Green for Injection, USP also has the property of being nearly 98% bound to blood protein.

13 NONCLINICAL TOXICOLOGY

13.1 Carcinogenesis, Mutagenesis, Impairment of Fertility

No studies have been performed to evaluate the carcinogenicity, mutagenicity, or impairment of fertility.

16 HOW SUPPLIED/STORAGE AND HANDLING

ICG for Injection Set is a kit (NDC 70599-424-02) containing one Indocyanine Green for Injection, USP kit (NDC 70100-424-02) and these Instructions For Use with the KARL STORZ ICG Imaging System.

The Indocyanine Green for Injection, USP kit (NDC 70100-424-02) contains six 25 mg Indocyanine Green for Injection, USP vials and six 10 mL Sterile Water for Injection, USP plastic vials:

NDC 70100-424-01 Indocyanine Green for Injection, USP vial. 25 mg fill in 25 mL vial.

NDC 63323-185-10 (or NDC 0409-4887-17) Sterile Water for Injection, USP, 10 mL fill in 10 mL plastic vials.

ICG for Injection Set

Distributed by:

KARL STORZ Endoscopy-America, Inc.
El Segundo, CA 90245 USA

50441

PRINCIPAL DISPLAY PANEL - KIT CARTON

Kit Carton Label

Front Panel

NDC 70599-424-02 PN: VTG0001

ICG for Injection Set

For Intravenous Administration 25 mg/Vial Kit Rx Only - Sterile

STORZ
KARL STORZ-ENDOSKOPE

Back Panel

NDC 70599-424-02 PN: VTG0001

ICG for Injection Set

Contents:
Six Indocyanine Green for Injection, USP vials (25 mg each)
Six Sterile Water for Injection, USP Vials (10 mL each)

Lot Code Area
No Print / No Coating

STORZ
KARL STORZ-ENDOSKOPE

For Intravenous Administration 25 mg/Vial Kit Rx Only - Sterile 06/2016

Left Panel

ICG for Injection Set

DIRECTIONS FOR USE ENCLOSED

CAUTION: To ensure accurate readings,
Indocyanine Green, USP dissolved in Sterile Water
for Injection, USP must be used within 6 hours.

STORAGE: Store at 20° to 25°C (68° to 77°F)
[See USP Controlled Room Temperature].

USAGE: See package insert for dosage information.

25 mg/Vial Kit

Right Panel

ICG for Injection Set

Distributed by:
KARL STORZ
Endoscopy-America, Inc.
2151 E. Grand Ave.
El Segundo, CA 90245
Phone: (800) 421-0837
Fax: (800) 321-1304
E-Mail: communications@karlstorz.com
Web: www.karlstorz.com

Rx Only

25 mg/Vial Kit

PRINCIPAL DISPLAY PANEL - VIAL

Vial Label

NDC 70100-424-01

Indocyanine Green
for Injection, USP

25 mg/Vial

For Intravenous Administration
After reconstitution, use within 6 hours.

Rx only Sterile

Distributed by Diagnostic Green LLC

50428

Lot. No.
Exp.

PRINCIPAL DISPLAY PANEL - STERILE WATER VIAL

Sterile Water Label

10 mL Single-dose

Sterile Water
for Injection, USP

FOR DRUG DILUENT USE

Rx only NDC 0409-4887-17

Contains no antimicrobial or other added
substance. Sterile, nonpyrogenic. Do not give
intravenously unless rendered nearly isotonic.

Hospira, Inc. RL-4428
Lake Forest, IL 60045 USA